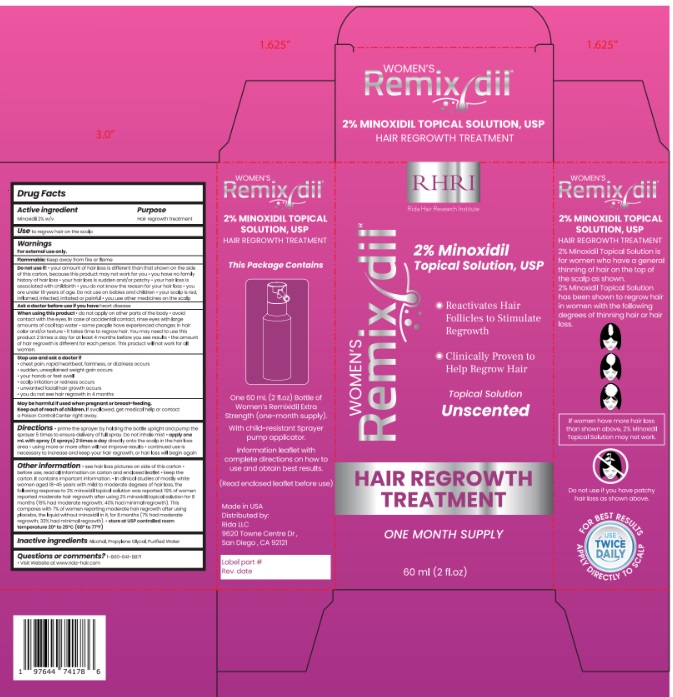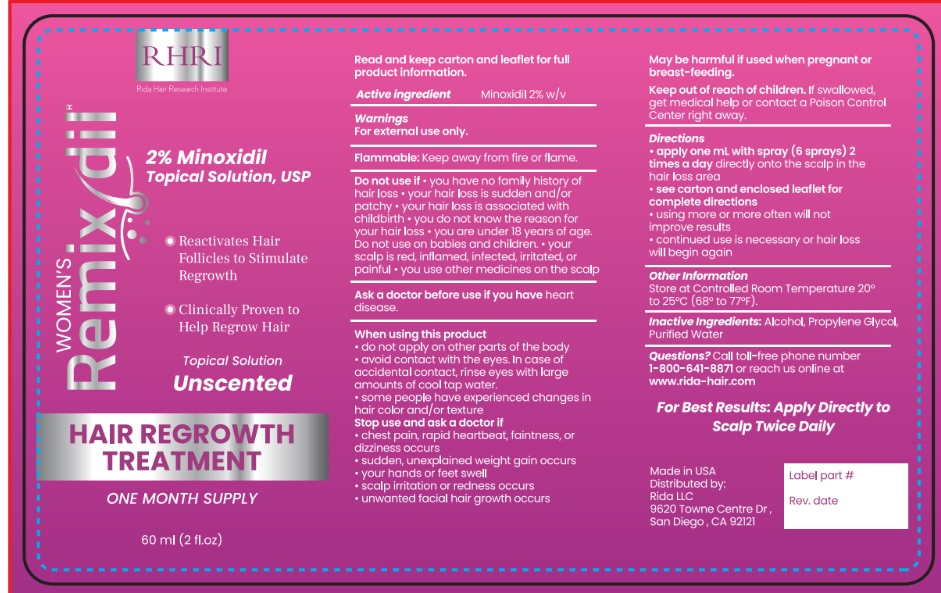 DRUG LABEL: REMIXDIL HAIR REGROWTH TREATMENT FOR WOMEN
NDC: 83004-009 | Form: SOLUTION
Manufacturer: Rida LLC
Category: otc | Type: HUMAN OTC DRUG LABEL
Date: 20250225

ACTIVE INGREDIENTS: MINOXIDIL 2 g/100 mL
INACTIVE INGREDIENTS: PROPYLENE GLYCOL; WATER; ISOPROPYL ALCOHOL

ACTIVE INGREDIENT

Minoxidil 2% w/v

USE

Use to regrow hair on the scalp

PURPOSE

Hair regrowth treatment

WARNINGS

For external use only.

Flamable: Keep away from fire of flame.

Do not use if:

- Your degree of hair loss is different than shown on the side of this carton, because this product may not work for you
- You have no family history of hair loss
- Your hair loss is sudden and/or patchy
- Your hair loss is associated with childbirth
- You do not know the reason for your hair loss
- You are under 18 years of age. Do not use on babies or children
- Your scalp is red, inflamed, infected, irritated, or painful
- You use other medicines on the scalp

Ask a doctor before use if you have heart disease

When using this product

- Do not apply on other parts of the body
- Avoid contact with the eyes. In case of accidental contact, rinse eyes with large amounts of cool tap water
- Some people have expereinced changes in hair color and/or texture
- It takes time to regrow hair. Results may occur at 2 months with twice a day usage. For some men, you may need to use this product for at least 4 months before you see results.
- The amount of hair regrowth is different for each person. This product will not work for everyone.

Stop use and ask a doctor if

- Chest pain, rapid heart beat, faintness, or dissiness occurs. Sudden, unexplained weight gain occurs
- Your hands or feet swell
- Scalp irritation or redness occurs
- You get unwanted facial hair growth
- You do not see hair regrowth in 4 months

PREGNANCY OR BREAST FEEDING

May be harmful if used when pregnant or breast-feeding.

Keep out of reach of children. If swallowed, get medical help or contact a Poison Control Center right away.

DIRECTIONS

- apply 1mL with dropper 2 times a day directly onto the scalp in the hair loss area
- using more or more often will not improve results
- continued use is necessary to increase and keep your hair regrowth, or hair loss will begin again

OTHER INFORMATION

- See hair loss pictures on the side of this carton
- Before use, read all information on carton and enclosed leaflet
- Keep the carton. It contains important information
- In clincial studies of mostly white women aged 18-45 years with moderate degrees of hair loss, the following responses to 2% minoxidil topical solution was reported: 19% of women reported moderate hair regrowth after using 2% minoxidil topical solution for 8 months (19% had moderate regrowth; 40% had minimal hair regrowth). This compares with the 7% of women reporting moderate hair regrowth after using a placebo, the liquid without minoxidil in it, for 8 months (7% had moderate regrowth; 33% had minimal regrowth).
- Store at controlled room temperature 20oto 25oC (68oto 77oF)

INACTIVE INGREDIENT

Alcohol, Propylene Glycol, Purified Water

Questions or comments? 1-800-641-8871
Visit website at www.rida-hair.com